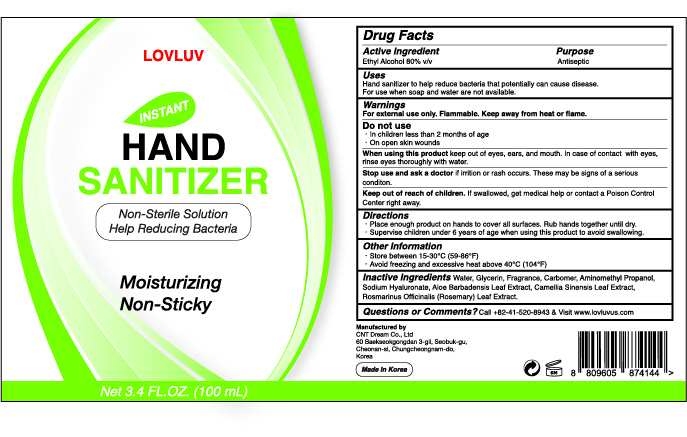 DRUG LABEL: LOVLUV Instant Hand Sanitizer
NDC: 71909-4144 | Form: LIQUID
Manufacturer: Cnt Dream. Co., Ltd
Category: otc | Type: HUMAN OTC DRUG LABEL
Date: 20200405

ACTIVE INGREDIENTS: ALCOHOL 80 mL/100 mL
INACTIVE INGREDIENTS: WATER 24.066 mL/100 mL

LOVLUV Instant Hand Sanitizer 3.4 FL.OZ. (100 mL)

Active Ingredient(s)

Alcohol 80% v/v. Purpose: Antiseptic

Purpose

Antiseptic, Hand Sanitizer

Use

Hand sanitizer to help reduce bacteria that potentially can cause disease.
For use when soap and water are not available.

Warnings

For external use only. Flammable. Keep away from heat or flame.

Do not use

• In children less than 2 months of age
• On open skin wounds

When using this product keep out of eyes, ears, and mouth. In case of contact with eyes, rinse eyes thoroughly with water.

Stop use and ask a doctor if irritation or rash occurs. These may be signs of a serious condition.

Keep out of reach of children. If swallowed, get medical help or contact a Poison Control Center right away.

Directions

- Place enough product on hands to cover all surfaces. Rub hands together until dry.
- Supervise children under 6 years of age when using this product to avoid swallowing.

Other information

- Store between 15-30℃ (59-86°F)
- Avoid freezing and excessive heat above 40℃ (104°F)

Inactive ingredients

Water, Glycerin, Fragrance, Carbomer, Aminomethyl Propanol, Sodium Hyaluronate, Aloe Barbadensis Leaf Extract, Camellia Sinensis Leaf Extract, Rosmarinus Officinalis (Rosemary) Leaf Extract.

Package Label - Principal Display Panel

LOVLUV
INSTANT HAND SANITIZER
Non-Sterile Solution
Help Reducing Bacteria
Moisturizing
Non-Sticky
Net 3.4 FL.OZ.(100 mL)